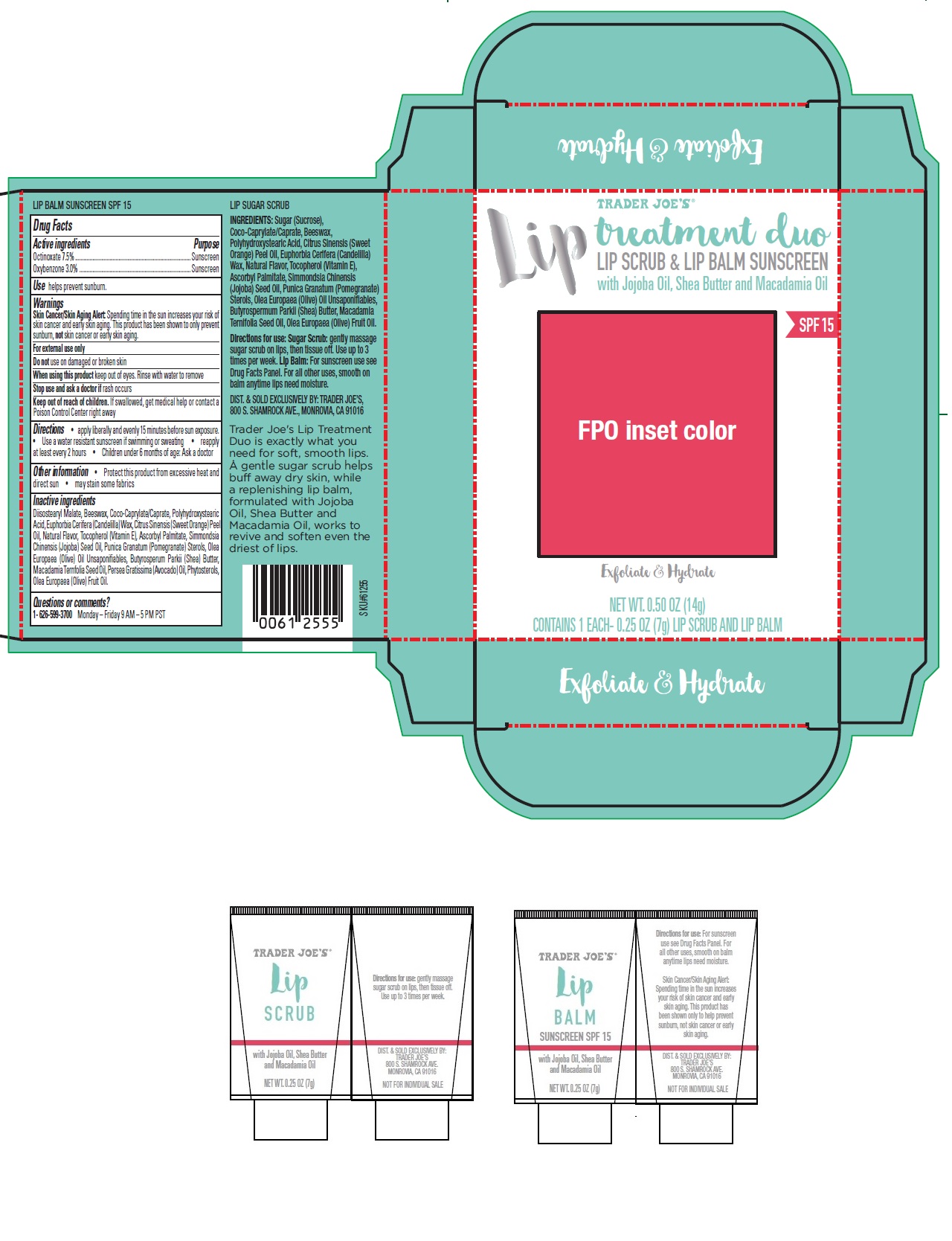 DRUG LABEL: LIP TREATMENT  DUO LIP SCRUB AND LIP BALM SUNSCREEN SPF 15
NDC: 71270-612 | Form: KIT | Route: TOPICAL
Manufacturer: Trader Joe's Company
Category: otc | Type: HUMAN OTC DRUG LABEL
Date: 20191031

ACTIVE INGREDIENTS: OCTINOXATE 7.5 g/100 g; OXYBENZONE 3.0 g/100 g
INACTIVE INGREDIENTS: DIISOSTEARYL MALATE; YELLOW WAX; COCO-CAPRYLATE/CAPRATE; POLYHYDROXYSTEARIC ACID (2300 MW); CANDELILLA WAX; ORANGE OIL; .ALPHA.-TOCOPHEROL; ASCORBYL PALMITATE; JOJOBA OIL; POMEGRANATE SEED OIL; OLEA EUROPAEA (OLIVE) OIL UNSAPONIFIABLES; SHEA BUTTER; MACADAMIA OIL; AVOCADO OIL; .BETA.-SITOSTEROL; OLIVE OIL

Lip treatment duo LIP SCRUB & LIP BALM SUNSCREEN SPF 15

Active ingredients

Octinoxate 7.5%

Oxybenzone 3.0%

Purpose

Sunscreen

Use

helps prevent sunburn.

Warnings

Skin Cancer/Skin Aging Alert: Spending time in the sun increases your risk of skin cancer and early skin aging. This product has been shown to only prevent sunburn, not skin cancer or early skin aging.

For external use only

Do not use on damaged or broken skin

When using this product keep out of eyes. Rinse with water to remove

Stop use and ask a doctor if rash occurs

Keep out of reach of children. If swallowed, get medical help or contact a Poison Control Center right away

Directions

• apply liberally and evenly 15 minutes before sun exposure. • Use a water resistant sunscreen if swimming or sweating • reapply
at least every 2 hours • Children under 6 months of age: Ask a doctor

Inactive ingredients

Diisostearyl Malate, Beeswax, Coco-Caprylate/Caprate, Polyhydroxystearic Acid, Euphorbia Cerifera (Candelilla) Wax, Citrus Sinensis (Sweet Orange) Peel Oil, Natural Flavor, Tocopherol (Vitamin E), Ascorbyl Palmitate, Simmondsia Chinensis (Jojoba) Seed Oil, Punica Granatum (Pomegranate) Sterols, Olea Europaea (Olive) Oil Unsaponifiables, Butyrosperum Parkii (Shea) Butter, Macadamia Ternfolia Seed Oil, Persea Gratissima (Avocado) Oil, Phytosterols, Olea Europaea (Olive) Fruit Oil.

Other information

• Protect this product from excessive heat and direct sun • may stain some fabrics

Questions or comments?

1- 626-599-3700 Monday – Friday 9 AM – 5 PM PST

Lip treatment duo

LIP SCRUB & LIP BALM SUNSCREEN SPF 15

with Jojoba Oil, Shea Butter and Macadamia Oil

Exfoliate & Hydrate
LIP SUGAR SCRUB

INGREDIENTS: Sugar (Sucrose), Coco-Caprylate/Caprate, Beeswax, Polyhydroxystearic Acid, Citrus Sinensis (Sweet Orange) Peel Oil, Euphorbia Cerifera (Candelilla) Wax, Natural Flavor, Tocopherol (Vitamin E), Ascorbyl Palmitate, Simmondsia Chinensis (Jojoba) Seed Oil, Punica Granatum (Pomegranate) Sterols, Olea Europaea (Olive) Oil Unsaponifiables, Butyrospermum Parkii (Shea) Butter, Macadamia Ternifolia Seed Oil, Olea Europaea (Olive) Fruit Oil.

Directions for use: Sugar Scrub: gently massage sugar scrub on lips, then tissue off. Use up to 3 times per week. Lip Balm: For sunscreen use see Drug Facts Panel. For all other uses, smooth on balm anytime lips need moisture.

DIST. & SOLD EXCLUSIVELY BY: TRADER JOE’S,
800 S. SHAMROCK AVE., MONROVIA, CA 91016

NOT FOR INDIVIDUAL SALE.

Trader Joe's Lip Treatment Duo is exactly what you need for soft, smooth lips. A gentle sugar scrub helps buff away dry skin, while a replenishing lip balm, formulated with Jojoba Oil, Shea Butter and Macadamia Oil, works to revive and soften even the driest of lips.